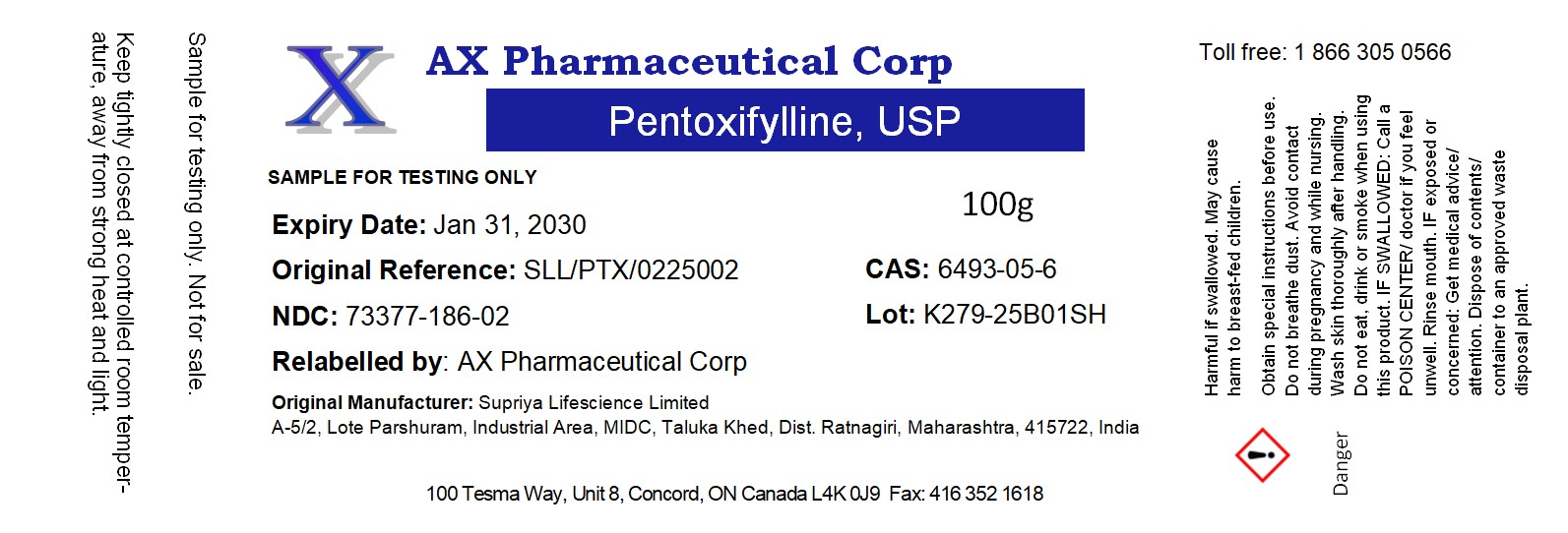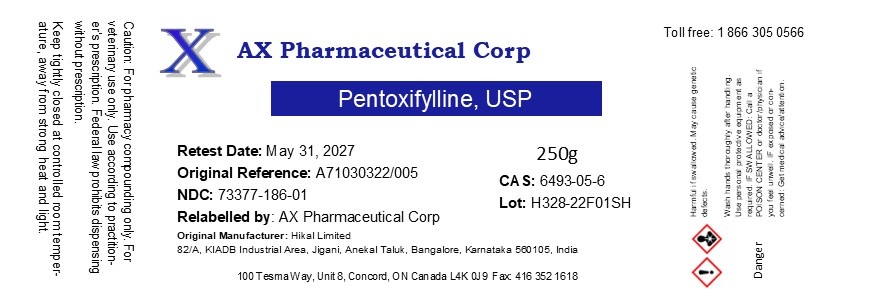 DRUG LABEL: Pentoxifylline
NDC: 73377-186 | Form: POWDER
Manufacturer: AX Pharmaceutical Corp
Category: other | Type: BULK INGREDIENT - ANIMAL DRUG
Date: 20251016

ACTIVE INGREDIENTS: PENTOXIFYLLINE 1 g/1 g

Pentoxifylline